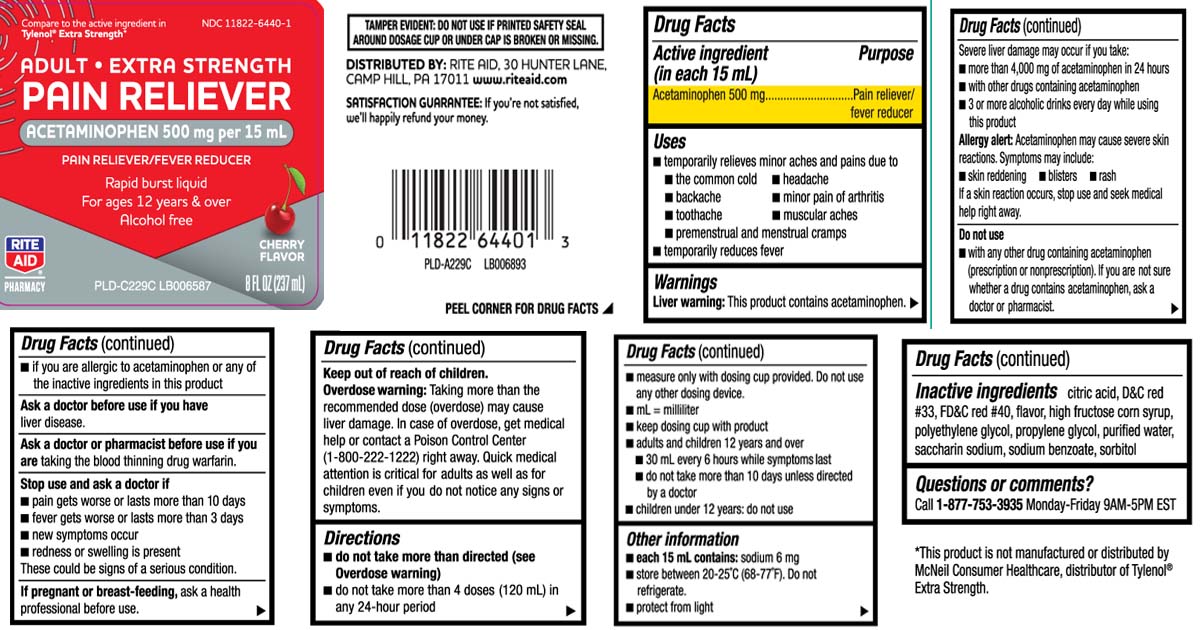 DRUG LABEL: Pain Reliever
NDC: 11822-6440 | Form: LIQUID
Manufacturer: Rite Aid Corporation
Category: otc | Type: HUMAN OTC DRUG LABEL
Date: 20250812

ACTIVE INGREDIENTS: ACETAMINOPHEN 500 mg/15 mL
INACTIVE INGREDIENTS: ANHYDROUS CITRIC ACID; D&C RED NO. 33; FD&C RED NO. 40; HIGH FRUCTOSE CORN SYRUP; POLYETHYLENE GLYCOL, UNSPECIFIED; PROPYLENE GLYCOL; WATER; SACCHARIN SODIUM; SODIUM BENZOATE; SORBITOL

Drug Facts

Active ingredient (in each 15 mL)

Acetaminophen 500 mg

Purpose

Pain reliever/fever reducer

Uses

- temporarily relieves minor aches and pains due to:
  - the common cold
  - headache
  - backache
  - minor pain of arthritis
  - toothache
  - muscular aches
  - premenstrual and menstrual cramps
- temporarily reduces fever

Warnings

Liver warning: This product contains acetaminophen. Severe liver damage may occur if you take:

- more than 4,000 mg of acetaminophen in 24 hours
- with other drugs containing acetaminophen
- 3 or more alcoholic drinks ever day while using this product

Allergy alert: Acetaminophen may cause severe skin reactions. Symptoms may include:

- skin reddening
- blisters
- rash

If a skin reaction occurs, stop use and seek medical help right away.

Do not use

- with any other drug containing acetaminophen (prescription or nonprescription). If you are not sure whether a drug contains acetaminophen, ask a doctor or pharmacist.
- if you are allergic to acetaminophen or any of the inactive ingredients in this product

Ask a doctor before use if you have

liver disease.

Ask a doctor or pharmacist before use if you are

taking the blood thinning drug warfarin.

Stop use and ask a doctor if

- pain gets worse or lasts for more than 10 days
- fever gets worse or lasts for more than 3 days
- new symptoms occur
- redness or swelling is present

These could be signs of a serious condition.

If pregnant or breast-feeding,

ask a health professional before use.

Keep out of reach of children.

Overdose warning: Taking more than the recommended dose (overdose) may cause liver damage. In case of overdose, get medical help or contact a Poison Control Center (1-800-222-1222) right away. Quick medical attention is critical for adults as well as for children even if you do not notice any signs or symptoms.

Directions

- do not take more than directed (see overdose warning)
- do not take more then 4 doses (120 mL) in any 24 hours period
- measure only with dosing cup provided. Do not use any other dosing device
- mL=milliliter
- keep dosing cup with product
- adults and children 12 years and over
  - 30 mL every 6 hours while symptoms last
  - do not take more than 10 days unless directed by a doctor
- children under 12 years: do not use

Other information

- each 15 mL contains:sodium 6 mg
- store between 20-25ºC (68-77ºF) do not refrigerate
- protect from light

Inactive ingredients

citric acid, D&C red 33, FD&C red 40, flavors, high fructose corn syrup, polyethylene glycol, propylene glycol, purified water, saccharin sodium, sodium benzoate, sorbitol

Questions or comments?

Call 1-877753-3935 Monday-Friday 9AM-5PM EST

Principal Display Panel

Compare to the active ingredient in Tylenol® Extra Strength*

ADULT • EXTRA STRENGTH

PAIN RELIEVER

ACETAMINOPHEN 500 mg per 15 mL

PAIN RELIEVER/FEVER REDUCER

Rapid burst liquid

For ages 12 years & over

Alcohol free

CHERRY FLAVOR

FL OZ (mL)

TAMPER EVIDENT: DO NOT USE IF PRINTED SAFETY SEAL AROUND DOSAGE CUP OR UNDER CAP IS BROKEN OR MISSING.

*This product is not manufactured or distributed by McNeil Consumer Healthcare, distributor of Tylenol® Extra Strength.

MANUFACTURED BY: RITE AID, 30 HUNTER LANE,

CAMP HILL, PA 17011

www.riteaid.com

Product Label

RITE AID PHARMACY Adult Extra Strength Pain Reliever Cherry Flavor